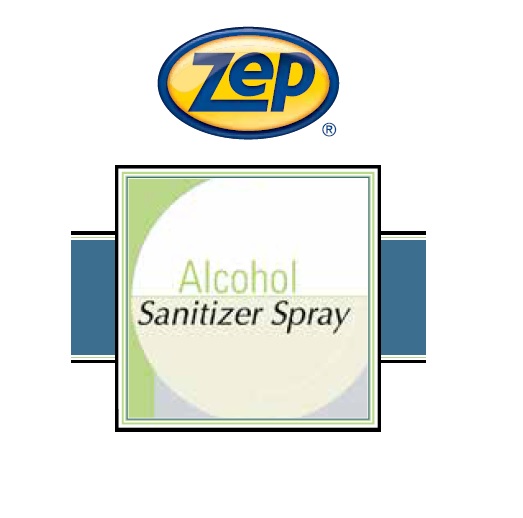 DRUG LABEL: Zep Alcohol Sanitizer
NDC: 66949-133 | Form: LIQUID
Manufacturer: Zep Inc.
Category: otc | Type: HUMAN OTC DRUG LABEL
Date: 20251226

ACTIVE INGREDIENTS: ALCOHOL 70 mL/100 mL
INACTIVE INGREDIENTS: WATER; GLYCERIN

66949-133 / 0900 Alcohol Sanitizer

Active ingredient

Ethanol 70% v/v

Purpose

Antiseptic

Uses

- Hand sanitizing to decrease bacteria on skin.
- No rinsing required.

Warnings

For external use only.
Do not use in the eyes; if in eyes, rinse promptly and thoroughly with water.
Flammable. Keep away from fire, flame or spark.

When using this product

- Do not swallow.
- If swallowed, do not induce vomiting and if individual is conscious, give large quantities of water to drink and consult a physician immediately.

Stop use and ask a doctor if skin irritation or redness persists for more than 72 hours.

Keep out of reach of children and pets. Children must be supervised in use of this product.

Directions

- Wet hands thoroughly with spray mist.
- Rub hands together allowing liquid to contact all areas, especially around the nails and cuticles.
- Continue rubbing vigorously until hands are dry.
- No rinsing or toweling is required.

Other information

Store at 4 to 27°C (40 to 80°F).

Dispose in accordance with all applicable federal, state and local regulations.

Inactive ingredients

Deionized water; Glycerine

Questions or comments?

Call 1-877-I-BUY-ZEP (1-877-428-9937)